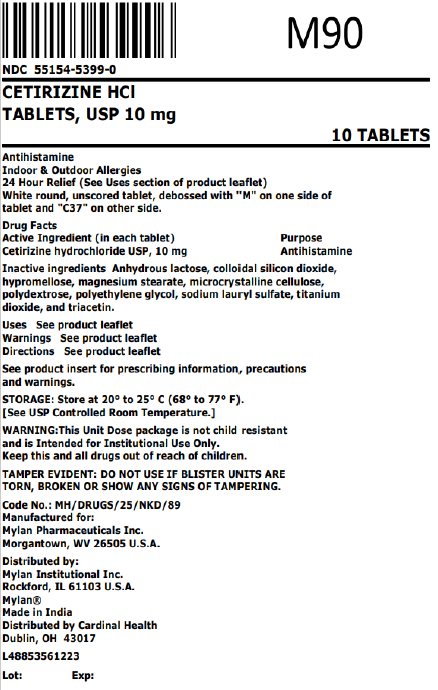 DRUG LABEL: Cetirizine Hydrochloride
NDC: 55154-5399 | Form: TABLET, FILM COATED
Manufacturer: Cardinal Health 107, LLC
Category: otc | Type: HUMAN OTC DRUG LABEL
Date: 20250926

ACTIVE INGREDIENTS: CETIRIZINE HYDROCHLORIDE 10 mg/1 1
INACTIVE INGREDIENTS: ANHYDROUS LACTOSE; SILICON DIOXIDE; HYPROMELLOSE, UNSPECIFIED; MAGNESIUM STEARATE; MICROCRYSTALLINE CELLULOSE; POLYDEXTROSE; POLYETHYLENE GLYCOL, UNSPECIFIED; SODIUM LAURYL SULFATE; TITANIUM DIOXIDE; TRIACETIN

Drug Facts

CETIRIZINE HCl
10 mg TABLETS, USP

Antihistamine

Indoor & Outdoor Allergies

TAMPER EVIDENT: DO NOT USE IF BLISTER UNITS ARE TORN, BROKEN OR SHOW ANY SIGNS OF TAMPERING.

Active ingredient (in each tablet)

Cetirizine Hydrochloride, USP 10 mg

Purpose

Antihistamine

Uses

temporarily relieves these symptoms due to hay fever or other upper respiratory allergies:

- runny nose
- sneezing
- itchy, watery eyes
- itching of the nose or throat

Warnings

Do not use

if you have ever had an allergic reaction to this product or any of its ingredients or to an antihistamine containing hydroxyzine.

Ask a doctor before use if you have

liver or kidney disease. Your doctor should determine if you need a different dose.

Ask a doctor or pharmacist before use if you are

taking tranquilizers or sedatives.

When using this product

- drowsiness may occur
- avoid alcoholic drinks
- alcohol, sedatives, and tranquilizers may increase drowsiness
- be careful when driving a motor vehicle or operating machinery

Stop use and ask a doctor if

an allergic reaction to this product occurs. Seek medical help right away.

If pregnant or breast-feeding:

- if breast-feeding: not recommended
- if pregnant: ask a health professional before use.

Keep out of reach of children.

In case of overdose, get medical help or contact a Poison Control Center right away.

Directions (24 Hour Relief)

adults and children 6 years and over | one 10 mg tablet once daily; do not take more than one 10 mg tablet in 24 hours. A 5 mg product may be appropriate for less severe symptoms.
adults 65 years and over | ask a doctor
children under 6 years of age | ask a doctor
consumers with liver or kidney disease | ask a doctor

Other information

- Store at 20° to 25°C (68° to 77°F). [See USP Controlled Room Temperature.]

Inactive ingredients

Anhydrous lactose, colloidal silicon dioxide, hypromellose, magnesium stearate, microcrystalline cellulose, polydextrose, polyethylene glycol, sodium lauryl sulfate, titanium dioxide, and triacetin

Questions? 1-800-848-0462

- Serious side effects associated with use of this product may be
  reported to this number.

HOW SUPPLIED

Cetirizine Hydrochloride Tablets, USP are available as follows:

10 mg - White, film-coated, round, biconvex, beveled
edge, unscored tablets debossed with M on one side of
the tablet and C37 on the other side.

Overbagged with 10 film-coated tablets per bag, NDC 55154-5399-0

WARNING: This Unit Dose package is not child resistant and is Intended for Institutional Use Only. Keep this and all drugs out of the reach of children.

Store at 20° to 25°C (68° to 77°F). [See USP Controlled Room Temperature.]

Manufactured for:
Mylan Pharmaceuticals Inc.
Morgantown, WV 26505 U.S.A.

Made in India

Code No.: MH/DRUGS/25/NKD/89

Distributed by:
Mylan Institutional Inc.
Rockford, IL 61103 U.S.A.

Distributed By:

Cardinal Health

Dublin, OH 43017

L48853561223

S-12769
10/21

Principal Display Panel

NDC 55154-5399-0

CETIRIZINE HCl

TABLETS, USP 10 mg

10 TABLETS